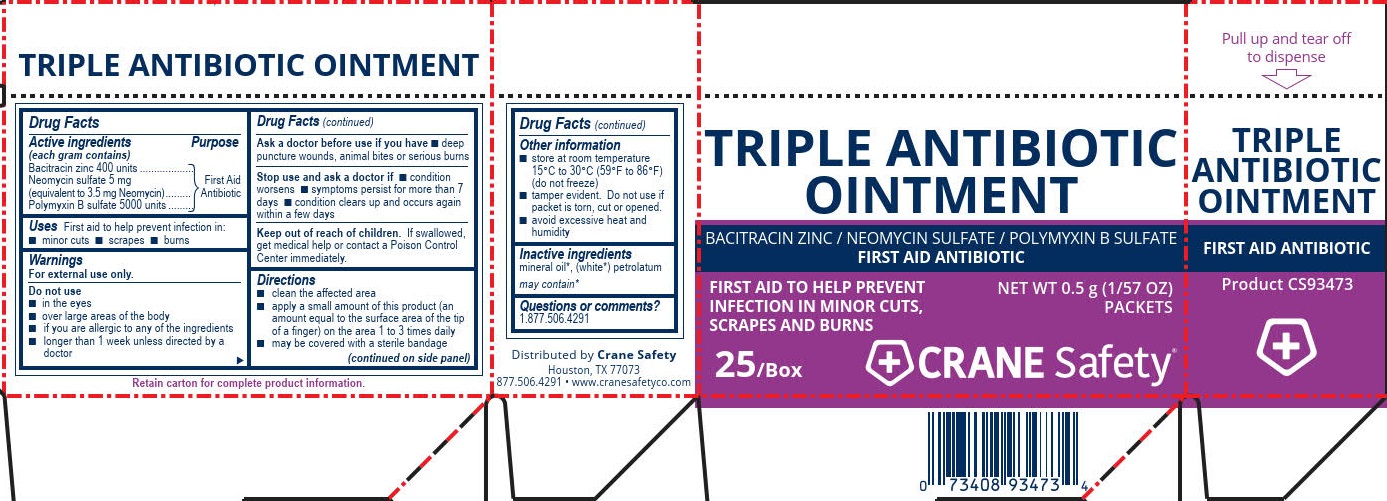 DRUG LABEL: Crane Safety Triple Antibiotic
NDC: 73408-930 | Form: OINTMENT
Manufacturer: Crane Safety LLC
Category: otc | Type: HUMAN OTC DRUG LABEL
Date: 20240117

ACTIVE INGREDIENTS: BACITRACIN ZINC 400 [USP'U]/1 g; POLYMYXIN B SULFATE 5000 [USP'U]/1 g; NEOMYCIN SULFATE 3.5 mg/1 g
INACTIVE INGREDIENTS: PETROLATUM

Crane Safety Triple Antibiotic Cream

Active ingredients (each gram contains)

Bacitracin zinc (400 units)

Neomycin sulfate 5 mg

(equivalent to 3.5 mg of Neomycin)

Polymyxin-B sulfate 5000 units

Purpose

First aid antibiotic

Uses

First aid to help prevent infection in:

- minor cuts
- scrapes
- burns

Warnings

For external use only.

Do not use

- in the eyes
- over large areas of the body
- if you are allergic to any of the ingredients
- longer than 1 week unless directed by a doctor

Ask a doctor before use if you have

- deep puncture wounds, animal bites, or serious burns

Stop use and ask a doctor if

- the condition persists or gets worse
- a rash or other allergic reaction develops

Keep out of reach of children. If swallowed, get medical help or contact a Poison Control Center immediately.

Directions

- clean the affected area
- apply a small amount of this product (an amount equal to the surface area of the tip of a finger) on the area 1 to 3 times daily
- may be covered with a sterile bandage

Other information

- store at room temperature 15°C to 30°C (59°F to 86°F) (do not freeze)
- tamper evident. Do not use if packet is torn, cut or opened.
- avoid excessive heat and humidity

Inactive ingredients

mineral oil*, (white*) petrolatum

may contain*

Questions or comments?

877.506.4291

Crane Safety Triple Antibiotic Label

Triple Antibiotic Ointment

Bacitracin Zinc / Neomycin Sulfate / Polymyxin B Sulfate

First Aid Antibiotic

First Aid to Help Prevent Infection in Minor Cuts, Scrapes and Burns

NET WT 0.5 g (1/57 oz) Packets

25/Box

CRANE Safety®

PACKAGE LABEL

Triple Antibiotic Ointment

Bacitracin Zinc / Neomycin Sulfate / Polymyxin B Sulfate

First Aid Antibiotic

First Aid to Help Prevent Infection in Minor Cuts, Scrapes and Burns

NET WT 0.5 g (1/57 oz) Packets

25/Box

CRANE Safety®